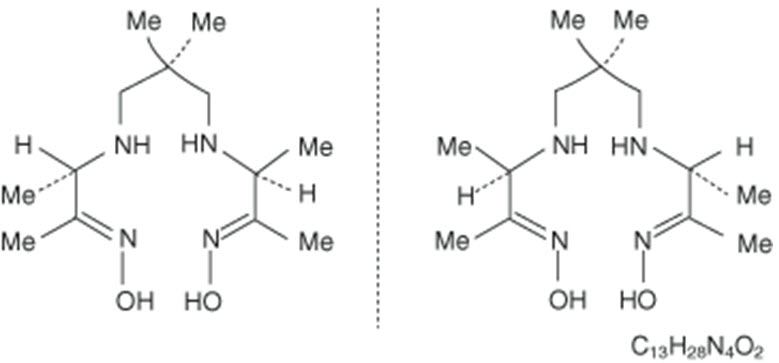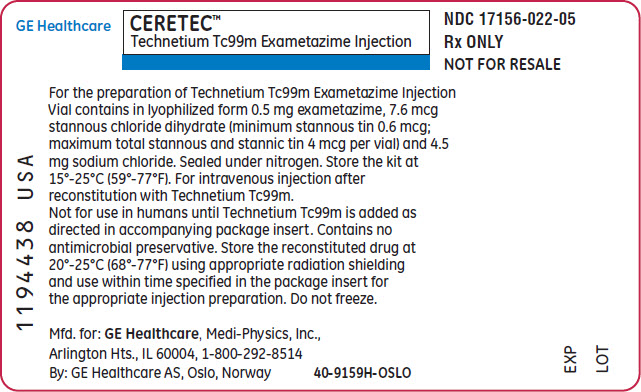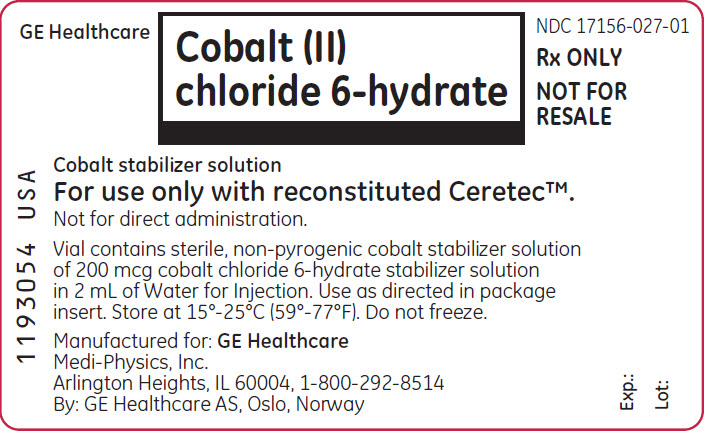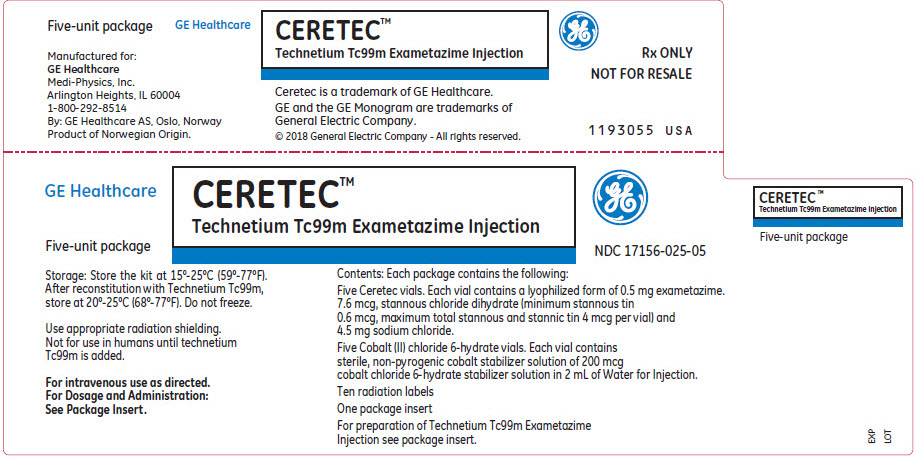 DRUG LABEL: Ceretec
NDC: 17156-025 | Form: KIT | Route: INTRAVENOUS
Manufacturer: Medi-Physics, Inc. dba GE Healthcare
Category: prescription | Type: HUMAN PRESCRIPTION DRUG LABEL
Date: 20240110

ACTIVE INGREDIENTS: Technetium Tc-99m Exametazime 0.5 mg/5 mL; Cobaltous Chloride 200 ug/2 mL
INACTIVE INGREDIENTS: Stannous Chloride 7.6 ug/5 mL; Sodium Chloride 4.5 mg/5 mL; Nitrogen; Water

HIGHLIGHTS OF PRESCRIBING INFORMATION

These highlights do not include all the information needed to use CERETEC safely and effectively. See full prescribing information for CERETEC.
CERETEC (kit for the preparation of technetium Tc 99m exametazime injection) for intravenous use.
Initial U.S. Approval: 1988

1 INDICATIONS AND USAGE

Ceretec is a radioactive diagnostic agent, indicated in adults and pediatric patients age 2 to 17 for:

- Leukocyte Labeled Scintigraphy – As an adjunct in the localization of intraabdominal infection and inflammatory bowel disease. (1.1)
- Cerebral Scintigraphy – As an adjunct in the detection of altered regional cerebral perfusion in stroke. (1.2)

2 DOSAGE AND ADMINISTRATION

- Do not use cobalt stabilizer solution for leukocyte labeled scintigraphy. (2.1)
- Use appropriate radiation safety measures and aseptic technique during preparation and handling. (2.1)
- Leukocyte Labeled Scintigraphy - The recommended adult dose is 185 MBq to 370 MBq (5 mCi to 10 mCi) of Tc 99m exametazime labeled leukocytes by intravenous injection. Administer as soon as possible after labeling, preferably within 20 minutes but no later than 1 hour. (2.2)
- Cerebral Scintigraphy - The recommended adult dose is 555 MBq to 1110 MBq (15 mCi to 30 mCi) by intravenous injection. (2.2)
- See full prescribing information for preparation and administration, interpretation of chromatograms and radiation dosimetry. (2)

3 DOSAGE FORMS AND STRENGTHS

Each Ceretec kit consists of 5 units. (3) Each unit contains:

- One vial of Ceretec: A lyophilized mixture of 0.5 mg exametazime and 4.5 mg sodium chloride.
- One vial of cobalt stabilizer solution: 200 mcg cobalt chloride 6-hydrate stabilizer solution in 2 mL of Water for Injection.

4 CONTRAINDICATIONS

None. (4)

5 WARNINGS AND PRECAUTIONS

Hypersensitivity reactions: Have cardiopulmonary resuscitation equipment and personnel available and monitor all patients for hypersensitivity reactions (5.1)

6 ADVERSE REACTIONS

Most common adverse reactions include a reversible increase in blood pressure. (6)

To report SUSPECTED ADVERSE REACTIONS, contact GE Healthcare at 1-800-654-0118 or FDA at 1-800-FDA-1088 or www.fda.gov/medwatch.

8 USE IN SPECIFIC POPULATIONS

- Pregnancy - Advise the pregnant woman of the potential risk to the fetus based on the radiation dose from the Technetium Tc 99m exametazime injection and the gestational timing of exposure. (8.1)
- Lactation – Temporarily discontinue breastfeeding. A lactating woman should pump and discard breastmilk for 12 to 24 hours after Technetium Tc 99m Exametazime labeled leukocyte administration. (8.2)

FULL PRESCRIBING INFORMATION

1 INDICATIONS AND USAGE

1.1 Leukocyte Labeled Scintigraphy

Ceretec, when reconstituted with technetium Tc 99m exametazime (without cobalt stabilizer solution), is indicated in adults and pediatric patients age 2 to 17 for leukocyte labeled scintigraphy as an adjunct in the localization of intraabdominal infection and inflammatory bowel disease.

1.2 Cerebral Scintigraphy

Ceretec, when reconstituted with technetium Tc 99m exametazime (with or without cobalt stabilizer solution), is indicated in adults and pediatric patients age 2 to 17 for cerebral scintigraphy as an adjunct in the detection of altered regional cerebral perfusion in stroke.

2 DOSAGE AND ADMINISTRATION

2.1 Important Preparation and Radiation Safety Instructions

- The Ceretec kit includes a cobalt stabilizer solution, which is optional for cerebral scintigraphy. DO NOT USE COBALT STABILIZER SOLUTION FOR LEUKOCYTE LABELED Scintigraphy [see Dosage and Administration (2.4, 2.6)].
- Technetium Tc 99m exametazime injection is a radioactive drug and should be handled with appropriate safety measures to minimize radiation exposure [see Warnings and Precautions (5.3)]. Use waterproof gloves and effective shielding, including syringe shields, when preparing and administering technetium Tc 99m exametazime injection.

2.2 Recommended Dosing and Imaging Procedures

Leukocyte Labeled Scintigraphy

Dosing

Adults: The recommended dose is 185 MBq to 370 MBq (5 mCi to 10 mCi) of Tc 99m exametazime labeled leukocytes by intravenous injection. Administer using a 19G needle as soon as possible, preferably within 20 minutes but no later than 1 hour, after preparing the Tc 99m labeled leukocyte suspension.

Pediatric patients age 2 to 17: The recommended dose is 7.4 MBq/kg (0.2 mCi/kg); with a minimum of 74 MBq (2 mCi). Do not exceed the maximum administered activity for an adult.

Imaging Procedures

- Instruct patients to empty their bladder prior to imaging.
- Dynamic imaging may be performed for the first 60 minutes after injection to assess lung clearance and to visualize cell migration.
- Perform static imaging at 0.5-1.5 hours, 2-4 hours and if necessary, at 18-24 hours after administration to detect focal accumulation of activity.

Cerebral Scintigraphy

Dosing

Adults: The recommended dose is 555 MBq to 1110 MBq (15 mCi to 30 mCi) by intravenous injection.

Pediatric patients age 2 to 17: The recommended dose is 14.0 MBq/kg (0.4 mCi/kg); with a minimum of 110 MBq (3.0 mCi). Do not exceed the maximum administered activity for an adult.

Imaging Procedures

- Images may be acquired by planar or SPECT imaging techniques.
- Perform imaging 30-90 min. after administration and complete imaging within 4 hrs after administration.

2.3 Preparation and Administration Instructions

General Preparation and Administration Instructions

- Use aseptic procedures throughout preparation and handling.
- Visually inspect the reconstituted technetium Tc 99m exametazime injection prior to use and do not use if there is evidence of particulate matter or discoloration.
- Measure patient dose with a dose calibrator immediately prior to administration.
- Instruct patients to maintain adequate hydration, after administration of technetium Tc 99m exametazime labeled white blood cells or Tc 99m exametazime injection and void frequently to minimize radiation dose to the kidneys and bladder [see Warnings and Precautions (5.3)].

Reconstitution Instructions

- Elute the technetium Tc 99m generator according to the manufacturer's instructions.
- Only use eluate from a technetium Tc 99m generator which has been eluted within the previous 24 hours.
- For the highest radiochemical purity reconstitute with freshly eluted technetium 99m generator eluate.
  - To prepare technetium Tc 99m exametazime injection for white blood cell labeling, use generator elute that is not more than 2 hours old.
  - To prepare technetium Tc 99m exametazime injection with cobalt stabilizer for cerebral imaging, use generator eluate that is not more than 4 hours old.

2.4 Preparation of Autologous Leukocytes

Leukocyte Harvest and Separation

1) Draw up 10 mL acid citrate dextrose solution into a 60 mL syringe.

2) Withdraw approximately 40 mL whole blood from the patient into the syringe using a 19-gauge butterfly needle infusion set. Close the syringe with a sterile hub.

3) Gently mix the contents of the syringe for 20 seconds.

4) Clamp the syringe barrel to the ring stand in an upright (hub side up) position and tilt the syringe 10-20 degrees from its position perpendicular to the bench.

5) Allow the red cells to sediment 30-60 minutes, until the supernatant [leukocyte rich plasma (LRP)] looks clear of red blood cells.

6) Using an infusion set, transfer the leukocyte-rich plasma (LRP), the supernatant, from the previous step, into a sterile, conical centrifuge tube marked "WBC" (white blood cell) and assure that only a minimum amount of red cells enter the centrifuge tube.

7) Immediately centrifuge the capped WBC tube at 400-450 g for 5 minutes. The plasma will separate out into a liquid [leukocyte poor plasma (LPP)] and a solid (WBC button). (Note: The button often contains a small number of red cells and may appear red).

8) Transfer the supernatant into another sterile tube marked "LPP" leaving enough supernatant to cover the white cell button.

Reserve LPP for later use (steps 11,15,18).

Washing and Radiolabeling

9) Add approximately 5 mL Sodium Chloride Injection, USP (0.9%) to the WBC button. Cap the "WBC" tube and resuspend the button by gently swirling.

10) Centrifuge the capped "WBC" tube at 150 g for 8 minutes and discard all but 0.5 to 1 mL of the supernatant to cover the cells.

11) Add 1 mL of "LPP" (from Step 9) to the white cell button and resuspend the cells by gentle swirling.

12) Reconstitute technetium Tc 99m exametazime from Ceretec with generator eluate [see Dosage and Administration (2.6)].

13) Within 30 minutes of preparation, add the reconstituted Tc 99m exametazime (do not use cobalt stabilizer solution) to the "WBC" tube. Swirl gently to mix.

14) Set a lab timer for 15 minutes and allow the white cells to incubate. Swirl at 30 second intervals during the incubation.

15) After incubation, add 10 mL of the LPP (from Step 9) to the "WBC" tube.

16) Cap the "WBC" tube, gently swirl, and then centrifuge at 450 g for 5 minutes.

17) Transfer the supernatant in the "WBC" tube into the "Wash" tube and leave the labeled white cells in the "WBC" tube.

18) Add approximately 5 mL of LPP (from Step 9) to the "WBC" tube. Gently swirl to resuspend the cells.

19) Draw the labeled cells into a syringe. Cap the syringe and assay the amount of radioactivity in a dose calibrator. Place the syringe in a shielded container.

20) Verify the identity of the labeled leukocyte recipient.

21) Administer the Tc 99m labeled leukocyte suspension using a 19G needle as soon as possible, preferably within 1-2 hours after labeling.

2.5 Preparation of Tc 99m Exametazime Injection with Cobalt Stabilizer Solution

- The preparation may be used in cerebral scintigraphy

1) Add up to 370 MBq to 2000 MBq (10 mCi to 54 mCi) sodium pertechnetate Tc 99m eluate to the shielded Ceretec vial.
2) Before reconstitution, the technetium Tc 99m generator eluate may be adjusted to the correct radioactive concentration [74 to 400 MBq/mL (2 to 10.8 mCi/mL)] by dilution with a volume of 5 mL preservative-free, non-bacteriostatic 0.9% sodium chloride for injection.
3) Between 1 and 5 minutes after reconstitution, inject 2 mL of cobalt stabilizer solution into the vial. Shake the shielded vial for 10 seconds to ensure complete mixing.
4) The cobalt stabilized technetium 99m exametazime is a pale straw-colored solution and the pH is in the range 5 to 8.
5) Use a Sample for Radiochemical Purity measurement.
6) Assay the vial for total radioactivity. Calculate the volume to be injected. Complete the label provided and attach to the vial.
7) Use the stabilized product within 5 hours after preparation. Individual patient doses may be stored aseptically in a capped syringe if required.
8) Discard any unused material.

Radiochemical Purity Measurement Tc 99m Exametazime Injection with Cobalt Stabilizer Solution

Obtain the Following Materials:

- Two GMCP-SA (Glass Microfiber Chromatography Paper impregnated with Silicic Acid) strips (2 cm (±2 mm) × 20 cm)
- Ascending chromatography development tanks
- MEK [methyl ethyl ketone (butanone)]
- 0.9 % sodium chloride

A combination of two chromatographic systems is necessary for the determination of the radiochemical purity of the injection:

- System 1 GMCP-SA: MEK [methyl ethyl ketone (butanone)]
- System 2 GMCP-SA:0.9% sodium chloride

Three potential radiochemical impurities may be present in prepared Technetium (99mTc) Exametazime Injection

- secondary Tc 99m exametazime complex
- free Tc 99m pertechnetate
- reduced-hydrolyzed Tc 99m

Method

1) Perform radiochemical purity testing as soon as possible after preparation.
2) Prepare the two Chromatographic Systems (System 1 and System 2).
3) Apply test samples by needle approximately 2.5 cm from the bottom of each GMCP-SA strip.
4) Immediately place each strip in prepared ascending chromatography development tanks. After the solvent has travelled to the 14 cm mark, remove the strips and mark the solvent fronts.
5) Allow the strips to dry.
6) Determine the distribution of activity determined using suitable equipment.
7) Chromatogram Interpretation:

System 1 (GMCP-SA: MEK [butanone])
Origin | Secondary Tc 99m exametazime complex and reduced-hydrolyzed Tc 99m
Migrate at Rf 0.8-1 | Lipophilic Tc 99m exametazime complex and Tc 99m pertechnetate

System 2 (GMCP-SA:0.9% sodium chloride)
Origin | Lipophilic Tc 99m exametazime complex, secondary Tc 99m exametazime complex, and reduced-hydrolyzed Tc 99m
Migrate at Rf 0.8-1 | Tc 99m pertechnetate

8) Calculate the percentage of activity due to both secondary Tc 99m exametazime complex and reduced-hydrolyzed Tc 99m from System 1 (A %).
9) Calculate the percentage of activity due to Tc 99m pertechnetate from System 2 (B %).
10) Calculate the radiochemical purity:
  % lipophilic Tc 99m exametazime complex = 100 - (A %+B %)
  - A % represents the level of secondary Tc 99m exametazime complex plus reduced-hydrolyzed Tc 99m.
  - B % represents the level of Tc 99m pertechnetate.

11) Do not use if radiochemical purity of lipophilic Tc 99m exametazime is less than 80%.

2.6 Preparation of Technetium Tc 99m Exametazime Injection Without Cobalt Stabilizer Solution

The preparation may be used in cerebral scintigraphy or for use in the preparation of Tc 99m labeled leukocytes.

1) Add 370 MBq to 2000 MBq (10 mCi up to 54 mCi) of sodium pertechnetate Tc 99m eluate.
2) Before reconstitution, the technetium Tc 99m generator eluate may be adjusted to the correct radioactive concentration [74 to 400 MBq/mL (2 to 10.8 mCi/mL)] by dilution with a volume of 5 mL preservative-free, non-bacteriostatic 0.9 % sodium chloride for injection.
3) The pH of the prepared injection is 9 to 9.8.
4) Use a sample for Radiochemical Purity Measurement.
5) Assay the total activity.
6) Calculate the volume to be injected and complete the label provided and attach to the vial shield.
7) Use the preparation within 30 minutes after reconstitution.
8) Discard any unused material.

Radiochemical Purity Measurement Tc 99m Exametazime Injection without Cobalt Stabilizer Solution

- Perform radiochemical purity testing of technetium Tc 99m exametazime within 2 minutes of reconstitution.
- The entire procedure takes approximately 15 minutes.

Obtain the Following Materials:

- 2 SA ITLC strips 20 cm × 2 cm
- 1 Whatman No. 1 strips 6 cm × 0.7 cm
- MEK (methyl ethyl ketone [butanone])
- 0.9% aqueous sodium chloride (non-bacteriostatic)
- 50% aqueous acetonitrile
- Dilute with non-bacteriostatic Water for Injection
- Glass test tubes (12 × 75 mm)
- Glass measuring cylinders (100 mL) with covers
- 1 mL syringes with 25-gauge needles

- A combination of 3 chromatographic systems is necessary for the complete definition of the radiochemical composition of the injection.
  - System 1: MEK (methyl ethyl ketone [butanone]) + SA ITLC strip
  - System 2: 0.9% non-bacteriostatic sodium chloride solution + SA ITLC strip
  - System 3: 50% acetonitrile solution + Whatman No. 1 paper strip

- Three potential radiochemical impurities may be present in the prepared injection of the lipophilic Tc 99m exametazime complex.
  - a secondary Tc 99m exametazime complex
  - free Tc 99m pertechnetate
  - reduced-hydrolyzed Tc 99m

Method

1) Prepare chromatography tubes (Identify the solvent in each cylinder).

System 1 - 100 mL cylinder containing a 1 cm depth of fresh MEK.
System 2 - 100 mL cylinder containing a 1 cm depth of 0.9% sodium chloride.
System 3 - 1 chromatography tube containing 0.2-0.3 mL of 50% acetonitrile, respectively.

2) Prepare 2 SA ITLC strips and 1 Whatman No. 1 paper strip.

Mark the SA ITLC strips 2.5 cm from the bottom as the point of origin.
Mark both the SA ITLC strips at 14 cm above the origin (solvent front).
Mark the Whatman strip 1 cm from the bottom as the point of origin.

3) Apply at least 5 microliter samples of freshly prepared Tc 99m exametazime solution to the origin of the 3 strips (within 2 minutes of reconstitution). Do not allow to dry.

4) Immediately place 1 SA ITLC strip into the MEK tank (System 1), the second SA ITLC strip into the saline tank (System 2), and the Whatman No. 1 paper strip into the 50% acetonitrile tube (System 3).

5) The SA ITLC MEK strip takes approximately 15 minutes to run. When the eluate has reached the solvent front remove the strip from the tube with forceps and immediately cut 1 cm above the origin.

6) The SA ITLC saline strip takes approximately 15 minutes to run. When the eluate has reached the solvent front remove the strip from the tube with forceps and immediately cut 2.5 cm above the origin.

7) The Whatman No. 1 paper CH3CN strip takes approximately 100 seconds to run. When the eluate has reached the solvent front mark remove the strip from the tube with forceps and immediately cut 0.5 cm above the origin.

8) Chromatogram Interpretation:

System 1 (SA ITLC: MEK (methyl ethyl ketone [butanone])
Origin | Secondary Tc 99m exametazime complex and reduced-hydrolyzed Tc 99m
Migrate at Rf 0.8-1 | Lipophilic Tc 99m exametazime complex and Tc 99m pertechnetate

System 2 (SA ITLC: 0.9% sodium chloride)
Origin | Lipophilic Tc 99m exametazime complex, secondary Tc 99m, exametazime complex and reduced-hydrolyzed Tc 99m
Migrate at Rf 0.8-1 | Tc 99m pertechnetate

System 3 (Whatman No. 1: 50% aqueous acetonitrile)
Origin | Reduced-hydrolyzed Tc 99m
Migrate at Rf 0.8-1 | Lipophilic Tc 99m exametazime complex, secondary Tc 99m exametazime complex and Tc 99m pertechnetate

9) Count the separate sections of each strip to determine the activity distribution. Calculate:

- % origin of saline strip (system 2)
- % origin of MEK strip (system 1)
- % solvent front of saline strip (= % Tc 99m pertechnetate)
- % origin of Whatman No. 1 paper strip (= % reduced-hydrolyzed Tc 99m)

10) Calculate Radiochemical Purity

% lipophilic Tc 99m exametazime complex = % origin of saline strip (system 2) – % origin of MEK strip (system 1)

11) Do not use if the radiochemical purity of the lipophilic Tc 99m exametazime complex is less than 80%.

2.7 Radiation Dosimetry

Tc 99m Exametazime labeled leukocytes for leukocyte labeled scintigraphy

Radiation absorbed dose per unit activity (microGy/MBq) administered to average-size adults (70 kg) and pediatric patients from an intravenous injection of Tc 99m Exametazime labeled leukocytes is estimated in Table 1.

Table 1: Estimated Radiation Absorbed Dose for Tc 99m exametazime labeled white blood cells (leukocytes)
Organ | Absorbed dose per unit activity administered (microGy / MBq)
Organ | Adult | 15 years | 10 years | 5 years | 1 year
Adrenals | 12 | 12 | 18 | 26 | 43
Bone surfaces | 16 | 21 | 34 | 61 | 150
Brain | 2.3 | 2.9 | 4.4 | 7 | 13
Breast | 2.4 | 2.9 | 4.9 | 7.6 | 13
Gallbladder wall | 8.4 | 10 | 16 | 25 | 36
Gastrointestinal tract
- Esophagus | 3.5 | 4.2 | 5.8 | 8.6 | 15
- Stomach wall | 8.1 | 9.6 | 14 | 20 | 32
- Small intestine wall | 4.6 | 5.7 | 8.7 | 13 | 21
- Colon wall | 4.3 | 5.4 | 8.4 | 12 | 21
- Upper large intestine wall | 4.7 | 5.9 | 9.3 | 14 | 23
- Lower large intestine wall | 3.7 | 4.8 | 7.3 | 10 | 18
Heart wall | 9.4 | 12 | 17 | 25 | 44
Kidneys | 12 | 14 | 22 | 32 | 54
Liver | 20 | 26 | 38 | 54 | 97
Lungs | 7.8 | 9.9 | 15 | 23 | 41
Muscles | 3.3 | 4.1 | 6 | 8.9 | 16
Ovaries | 3.9 | 5 | 7.2 | 11 | 18
Pancreas | 13 | 16 | 23 | 34 | 53
Red marrow | 23 | 25 | 40 | 71 | 140
Skin | 1.8 | 2.1 | 3.4 | 5.5 | 10
Spleen | 150 | 210 | 310 | 480 | 850
Testes | 1.6 | 2.1 | 3.2 | 5.1 | 9.2
Thymus | 3.5 | 4.2 | 5.8 | 8.6 | 15
Thyroid | 2.9 | 3.7 | 5.8 | 9.3 | 17
Urinary bladder wall | 2.6 | 3.5 | 5.2 | 7.8 | 14
Uterus | 3.4 | 4.3 | 6.5 | 9.7 | 16
Remaining organs | 3.4 | 4.2 | 6.3 | 9.5 | 16
Effective dose per unit activity | 11 microSv/MBq | 14 microSv/MBq | 22 microSv/MBq | 34 microSv/MBq | 62 microSv/MBq
*International Commission on Radiological Protection, Radiation Dose to Patients from Radiopharmaceuticals: A Compendium of Current Information Related to Frequently Used Substances, Ann ICRP 2015)., ICRP Publication 128, Ann ICRP 2015).

Tc 99m Exametazime Injection for Cerebral Scintigraphy

Based on human data, the radiation absorbed doses to average sized adults (70kg) and pediatric patients from an intravenous injection of Tc 99m exametazime injection are estimated in Table 2.

Table 2: Estimated Radiation Absorbed Dose for Tc 99m Exametazime Injection
Organ | Absorbed dose per unit activity administered (microGy / MBq)
Organ | Adult | 15 years | 10 years | 5 years | 1 year
Adrenals | 5.3 | 6.7 | 9.9 | 14 | 24
Bone surfaces | 5.1 | 6.4 | 9.4 | 14 | 24
Brain | 6.8 | 11 | 16 | 21 | 37
Breast | 2 | 2.4 | 3.7 | 5.6 | 9.5
Gallbladder wall | 18 | 21 | 28 | 48 | 140
Gastrointestinal tract
- Esophagus | 2.6 | 3.3 | 4.7 | 6.9 | 11
- Stomach wall | 6.4 | 8.5 | 12 | 19 | 36
- Small intestine wall | 12 | 15 | 24 | 36 | 65
- Colon wall | 17 | 22 | 35 | 55 | 100
- Upper large intestine wall | 18 | 24 | 38 | 60 | 110
- Lower large intestine wall | 15 | 19 | 31 | 48 | 90
Heart wall | 3.7 | 4.7 | 6.7 | 9.7 | 16
Kidneys | 34 | 41 | 57 | 81 | 140
Liver | 8.6 | 11 | 16 | 23 | 40
Lungs | 11 | 16 | 22 | 34 | 63
Muscles | 2.8 | 3.5 | 5 | 7.3 | 13
Ovaries | 6.6 | 8.3 | 12 | 17 | 27
Pancreas | 5.1 | 6.5 | 9.7 | 14 | 23
Red marrow | 3.4 | 4.1 | 5.9 | 8 | 14
Skin | 1.6 | 1.9 | 2.9 | 4.5 | 8.3
Spleen | 4.3 | 5.4 | 8.2 | 12 | 20
Testes | 2.4 | 3 | 4.4 | 6.1 | 11
Thymus | 2.6 | 3.3 | 4.7 | 6.9 | 11
Thyroid | 26 | 42 | 63 | 140 | 260
Urinary bladder wall | 23 | 28 | 33 | 33 | 56
Uterus | 6.6 | 8.1 | 12 | 15 | 25
Remaining organs | 3.2 | 4 | 6 | 9.2 | 17
Effective dose per unit activity | 9.3 microSv/MBq | 11 microSv/MBq | 17 microSv/MBq | 27 microSv/MBq | 49 microSv/MBq
*International Commission on Radiological Protection, Radiation Dose to Patients from Radiopharmaceuticals: A Compendium of Current Information Related to Frequently Used Substances, Ann ICRP 2015)., ICRP Publication 128, Ann ICRP 2015).

The effective dose resulting from the administration of a (maximal recommended) activity of 1110 MBq for an adult weighing 70 kg is about 10.3 mSv. For an administered activity of 740 MBq the typical radiation dose to the target organ (brain) is 5 mGy and the typical radiation dose to the critical organ (kidneys) is 25 mGy.

3 DOSAGE FORMS AND STRENGTHS

The Ceretec Kit is supplied as a five-unit package. Each unit contains:

- One (10 mL, multiple-dose) vial of Ceretec: A lyophilized mixture of 0.5 mg exametazime, sealed under nitrogen atmosphere with a rubber closure.
- One vial cobalt stabilizer solution: 200 mcg cobaltous chloride 6-hydrate stabilizer solution in 2 mL of Water for Injection.

4 CONTRAINDICATIONS

None

5 WARNINGS AND PRECAUTIONS

5.1 Hypersensitivity Reactions

Hypersensitivity reactions have been reported following the administration of Tc 99m exametazime injection and Tc 99m exametazime labeled leukocytes including serious signs and symptoms of anaphylaxis following administration [see Adverse Reactions (6)]. Always have cardiopulmonary resuscitation equipment and personnel available and monitor all patients for hypersensitivity reactions.

5.2 Risk for Image Interpretation Errors

The interpretation of images for leukocyte labeled imaging can be affected by the presence of other pathophysiological processes such as: tumor, infarction, trauma, and inflammatory conditions.

5.3 Radiation Exposure Risk

Technetium Tc 99m contributes to a patient's overall long-term cumulative radiation exposure, which is associated with an increased risk of cancer. Ensure safe handling and preparation procedures to protect patients and health care workers from unintentional radiation exposure. Encourage patients to drink fluids and instruct patients to void when the examination is completed and as often thereafter as frequently as possible after administration [see Dosage and Administration (2.1, 2.3)]. Radiation risks associated with the use of Tc 99m exametazime injection and Tc 99m exametazime labeled leukocytes are greater in pediatric patients than in adults due to greater radiosensitivity and longer life expectancy.

6 ADVERSE REACTIONS

The following serious adverse reactions are described elsewhere in the labeling:

- Hypersensitivity Reactions [see Warnings and Precautions (5.1)].

The following adverse reactions associated with the use of Ceretec were identified in clinical studies or postmarketing reports. Because some of these reactions were reported voluntarily from a population of uncertain size, it is not always possible to reliably estimate their frequency or establish a causal relationship to drug exposure.

Cardiovascular disorders: Reversible increase in blood pressure, flushing

Gastrointestinal disorders: Nausea, vomiting

General disorders and administration site conditions: Malaise, fatigue, fever

Immune system disorders: Hypersensitivity reactions: anaphylactic reactions including shock, facial edema, rash, pruritus or erythema

Nervous system disorders: Headache, dizziness, paresthesia

8 USE IN SPECIFIC POPULATIONS

8.1 Pregnancy

Risk Summary

Limited available data with technetium Tc 99m exametazime use in pregnant women are insufficient to inform any drug associated risks for major birth defects and miscarriage. Technetium Tc 99m exametazime is transferred across the placenta [see Data]. Animal reproduction studies with technetium Tc 99m exametazime have not been conducted. However, all radiopharmaceuticals have the potential to cause fetal harm depending on the fetal stage of development and the magnitude of the radiation dose. If considering technetium Tc 99m exametazime administration to a pregnant woman, inform the patient about the potential for adverse pregnancy outcomes based on the radiation dose from technetium Tc 99m exametazime and the gestational timing of exposure.

The estimated background risk of major birth defects and miscarriage for the indicated population is unknown. All pregnancies have a background risk of birth defect, loss, or other adverse outcomes. In the U.S. general population, the estimated background risk of major birth defects and miscarriage in clinically recognized pregnancies is 2-4% and 15-20%, respectively.

Data

Human Data

Limited published literature describes Tc 99m exametazime crossing the placental barrier and visualization of radioactivity in the fetal liver. No adverse fetal effects or radiation-related risks have been identified for diagnostic procedures involving less than 50 mGy, which represents less than 10 mGy fetal doses.

8.2 Lactation

Risk Summary

There are limited data available in the scientific literature on the presence of technetium Tc 99m exametazime in human milk. There are no data available regarding the effects of technetium Tc 99m exametazime on the breastfed infant or on milk production. Exposure of technetium Tc 99m exametazime to a breast fed infant can be minimized by temporary discontinuation of breastfeeding [see Clinical Considerations]. The developmental and health benefits of breastfeeding should be considered along with the mother's clinical need for Ceretec and any potential adverse effects on the breastfed child from Ceretec or from the underlying maternal condition.

Clinical Considerations

To decrease radiation exposure to the breastfed infant, advise a lactating woman to pump and discard breast milk after the administration of technetium Tc 99m exametazime injection or technetium Tc 99m exametazime-labeled leukocytes for 12 to 24 hours, where the duration corresponds to the typical range of administered activity, 259 MBq to 925 MBq (7 mCi to 25 mCi).

8.4 Pediatric Use

Ceretec is indicated for use in pediatric patients from 2 to 17 years of age for leukocyte labelled scintigraphy and brain scintigraphy. The use of Ceretec for leukocyte labelled scintigraphy and brain scintigraphy is supported by extrapolation from clinical effectiveness in adults. The safety and dosing recommendations are based on clinical experience.

Safety and effectiveness in pediatric patients less than 2 years of age have not been established.

8.5 Geriatric Use

Clinical studies of Ceretec did not include sufficient numbers of subjects aged 65 and over to determine whether they respond differently from younger subjects. Other reported clinical experience has not identified differences in responses between the elderly and younger patients. In general, dose selection for an elderly patient should be cautious, usually starting at the low end of the dosing range, reflecting the greater frequency of decreased hepatic, renal or cardiac function, and of concomitant disease or other drug therapy.

8.6 Renal Impairment

This drug is known to be substantially excreted by the kidney, and radiation exposure may be greater in patients with impaired renal function. A reduction in administered Tc 99m can be considered provided an adequate number of leukocytes are administered.

11 DESCRIPTION

11.1 Chemical Characteristics

Ceretec (kit for the preparation of technetium Tc 99m exametazime injection) prepares a radioactive diagnostic agent for intravenous use.

Each unit consists of the following:

- One 10 mL vial of exametazime containing a sterile, non-pyrogenic, lyophilized mixture of 0.5 mg exametazime, 7.6 mcg stannous chloride dihydrate (minimum stannous tin 0.6 mcg; maximum total stannous and stannic tin 4 mcg per vial) and 4.5 mg sodium chloride, sealed under nitrogen atmosphere with a rubber closure. The product contains no antimicrobial preservative.
- One vial of cobalt stabilizer containing a sterile, non-pyrogenic solution of 200 mcg cobaltous chloride 6-hydrate in 2 mL of Water for Injection.

The chemical name for Exametazime is [(RR,SS)-4.8-diaza-3,6,6,9-tetramethylundecane-2, 10-dione bisoxime]. The molecular formula of exametazime is C13H28N4O2, with the following structural formula:

Prior to publication of the USAN, exametazime was known as hexamethylpropylene amine oxime (HM-PAO). The name HM-PAO appears in many publications.

When sterile pyrogen-free sodium pertechnetate Tc 99m in isotonic saline is added to the vial of exametazime, a Tc 99m complex of exametazime is formed.

11.2 Physical Characteristics

Technetium Tc 99m decays by isomeric transition with a physical half-life of 6 hours. Photons that are useful for imaging studies are listed in Table 3.

Table 3: Principal Radiation Emission Data-technetium Tc 99m
Radiation | Mean % Disintegration | Mean Energy (keV)
Gamma 2 | 88.5 | 140.5

11.3 External Radiation

The air-kerma-rate (exposure-rate) constant for technetium Tc 99m is 5.23 m^2∙pGy∙(MBq)^–1∙s^–1 [0.795 cm^2∙R∙(mCi)^–1∙h^–1]. The first half-value thickness of lead (Pb) for technetium Tc 99m is 0.25 mm. A range of values for the relative attenuation of the radiation emitted by this radionuclide that results from interposition of various thicknesses of Pb is shown in Table 4. For example, the use of a 3 mm thickness of Pb will decrease the external radiation exposure by a factor of approximately 1,000.

Table 4: Radiation Attenuation by Lead Shielding
Shield Thickness (Pb) mm | Coefficient of Attenuation
0.25 | 0.5
1 | 10^–1
2 | 10^–2
3 | 10^–3
4 | 10^–4
5 | 10^–5

To correct for physical decay of this radionuclide, the fractions that remain at selected intervals relative to the time of calibration are shown in Table 5.

Table 5: Physical Decay Chart – Tc 99m half-life 6.03 hours
Hours | Fraction Remaining | Hours | Fraction Remaining
0 [Calibration time (time of preparation)] | 1 | 7 | 0.447
1 | 0.891 | 8 | 0.399
2 | 0.795 | 9 | 0.355
3 | 0.708 | 10 | 0.317
4 | 0.631 | 11 | 0.282
5 | 0.563 | 12 | 0.252
6 | 0.502 | 24 | 0.063

12 CLINICAL PHARMACOLOGY

12.1 Mechanism of Action

General

When technetium Tc 99m pertechnetate is added to exametazime in the presence of stannous reductant, a lipophilic technetium Tc 99m complex is formed. This lipophilic complex is the active moiety and is able to cross the blood-brain barrier as well as penetrate cell membranes to label leukocytes. It converts to a polar hydrophilic species at approximately 12% per hour. The polar hydrophilic species is unable to cross the blood-brain barrier or cell membranes.

Mechanism for Labeling Leukocytes

When incubated with leukocytes, which have been isolated from whole blood, the technetium Tc 99m exametazime complex, being lipid-soluble, penetrates the cell membrane of the leukocytes by passive diffusion. The lipophilic complex is then converted to a polar hydrophilic species, in a process possibly involving intracellular glutathione, thus trapping the technetium Tc 99m label within the cells.

Mechanism for Brain Uptake

The agent localizes in the brain as a function of regional cerebral perfusion. Technetium Tc 99m exametazime is primarily extracted and trapped by cerebral gray matter and the basal ganglia during the first pass through the brain. It has been proposed that the retention in the brain of technetium Tc 99m exametazime results from in vivo conversion of the primary complex to a less lipophilic complex, which is unable to cross the blood-brain barrier.

12.2 Pharmacodynamics

The relationship between Tc 99m exametazime plasma concentrations and successful imaging is not known.

12.3 Pharmacokinetics

Distribution

Leukocytes Labeled with Tc 99m Exametazime

During the first hour following injection of Tc 99m labeled leukocytes, activity is seen in the lungs, liver, spleen, blood pool, bone marrow, kidneys, gall bladder, and urinary bladder. At 4 hours following injection, lung radioactivity was decreased and bone marrow radioactivity was increased.

The lipophilic Tc 99m exametazime complex (that is not stabilized by cobalt chloride) is taken up by leukocytes and selectively retained in neutrophils. Label elution rate is up to 10% in the first hour.

Tc 99m Exametazime Injection

Studies in normal volunteers have shown that the technetium Tc 99m exametazime is rapidly cleared from the blood after intravenous injection. Uptake in the brain reaches a maximum of 3.5 to 7% of the injected dose within one minute of injection. Up to 15% of the activity is eliminated from the brain by 2 minutes post injection, after which little activity is lost for the following 24 hours except by physical decay of technetium Tc 99m.

Elimination

Excretion

Leukocytes Labeled with Tc 99m Exametazime

Following injection of Tc 99m labeled leukocytes, over the first 1 to 6 hours, the Tc 99m is visualized in the bowel. At 24 hours post-injection substantial colonic activity is seen, implying that excretion of radioactivity takes place through bowel.

Tc 99m Exametazime Injection

About 30% of the injected dose is found in the gastrointestinal tract immediately after injection and about 50% of this is excreted through the intestinal tract over 48 hours. About 40% of the injected dose is excreted through the kidneys and urine over the 48 hours after injection.

The use of cobalt stabilizer solution for stabilization prior to injection does not appear to affect the pharmacokinetic handling or distribution of Tc 99m exametazime.

13 NONCLINICAL TOXICOLOGY

13.1 Carcinogenesis, Mutagenesis, Impairment of Fertility

Ceretec without cobalt stabilizer solution

Long term animal studies have not been performed to evaluate carcinogenic potential or whether exametazime affects fertility in males or females. When evaluated in the Ames test, exametazime increased the apparent rate of gene mutation in the TA100 strain of S. typhimurium. Exametazime did not cause chromosomal aberrations in vitro (Chinese Hamster Ovary cells) or in vivo (rat bone marrow).

Ceretec with cobalt stabilizer solution

In-vitro mutagenicity studies indicate that the stabilized formulation of technetium-99m exametazime is weakly mutagenic in the Ames (bacterial mutation) test, human lymphocyte chromosome aberration assay and mouse lymphoma thymidine kinase assay.

The stabilized formulation is not mutagenic in two in-vivo assays (rat bone marrow micronucleus and rat liver micronucleus).

14 CLINICAL STUDIES

Two clinical trials were performed in a total of 88 patients who had suspected intra-abdominal infection or inflammation. Subjects received both Tc 99m labeled leukocytes and a radiolabeled comparator. Images were obtained at 2 and 30 minutes and at 2 and 4 hours and 24 hours. In two other clinical trials, in a total of 127 patients with suspected abdominal inflammation or infection received Tc 99m labeled leukocytes. Imaging was at 24 hours in one study and at 1, 3 and 24 hours in the other. In all four studies images were blindly evaluated and the findings were confirmed by surgery, biopsy or other clinical data.

Based on the above 4 studies, between 2 to 4 hours Tc 99m labeled leukocytes had 95-100% sensitivity and 62-85% specificity. In all studies, the false positive and false negatives relate to the bowel background, the location of the site of infection/inflammation and whether or not it is contiguous with the bowel. Images obtained at 24 hours can be unreliable because of a high bowel background; false negatives were noted in both Tc 99m and the radiolabeled comparator.

Other studies suggest that the interpretation of the images could be affected by the presence of tumors, infarction and peritonitis; liver abscess may be missed because of the bowel background.

16 HOW SUPPLIED/STORAGE AND HANDLING

16.1 How supplied

Each Ceretec Kit (NDC 17156-025-05) contains:

- Five 10mL vials of 0.5 mg exametazime
- Five 10mL vials of 200 mcg Cobalt stabilizer solution
- Ten radiation labels
- One package insert

Sodium Pertechnetate Tc 99m is not part of the Ceretec kit. Before reconstitution and radiolabeling with Tc 99m, the contents of the kit are not radioactive.

16.2 Storage and Handling

Store Ceretec kits at controlled room temperature 15°C to 25°C (59°F to 77°F).

This reagent kit is approved for use by persons licensed by the U.S. Nuclear Regulatory Commission or the relevant Agreement State. Store and dispose of technetium Tc 99m exametazime in compliance with the regulations of the government agency authorized to license the use of this radionuclide.

17 PATIENT COUNSELING INFORMATION

Administration Instructions

Instruct patients to remain hydrated and void frequently following administration to decrease radiation exposure [see Dosage and Administration (2.3)].

Pregnancy

Advise pregnant women of the risk of fetal exposure to radiation doses if they undergo a radionuclide imaging study [see Use in Specific Populations (8.1)].

Lactation

Advise a lactating woman to pump and discard breast milk for 12-24 hours (based on injection dose) after administration to minimize radiation exposure to the breastfed infant [see Use in Specific Populations (8.2)].

Distributed by:
GE Healthcare
Medi-Physics, Inc.
Arlington Heights, IL 60004

Manufactured by:
GE Healthcare AS
Oslo, Norway

Product of Norwegian Origin.

Ceretec is a trademark of GE Healthcare.

GE and the GE Monogram are trademarks of General Electric Company.

© 2018 General Electric Company - All rights reserved.

Patent No. 4,789,736

PRINCIPAL DISPLAY PANEL - 5 mL Vial Label

GE Healthcare

CERETEC™
Technetium Tc99m Exametazime Injection

NDC 17156-022-05
Rx ONLY
NOT FOR RESALE

For the preparation of Technetium Tc99m Exametazime Injection
Vial contains in lyophilized form 0.5 mg exametazime, 7.6 mcg
stannous chloride dihydrate (minimum stannous tin 0.6 mcg;
maximum total stannous and stannic tin 4 mcg per vial) and 4.5
mg sodium chloride. Sealed under nitrogen. Store the kit at
15°-25°C (59°-77°F). For intravenous injection after
reconstitution with Technetium Tc99m.
Not for use in humans until Technetium Tc99m is added as
directed in accompanying package insert. Contains no
antimicrobial preservative. Store the reconstituted drug at
20°-25°C (68°-77°F) using appropriate radiation shielding
and use within time specified in the package insert for
the appropriate injection preparation. Do not freeze.

Mfd. for: GE Healthcare, Medi-Physics, Inc.,
Arlington Hts., IL 60004, 1-800-292-8514
By: GE Healthcare AS, Oslo, Norway
40-9159H-OSLO

1194438 USA

EXP

LOT

PRINCIPAL DISPLAY PANEL - 2.5 mL Vial Label

GE Healthcare

Cobalt (II)
chloride 6-hydrate

NDC 17156-027-01
Rx ONLY
NOT FOR
RESALE

Cobalt stabilizer solution
For use only with reconstituted Ceretec™.
Not for direct administration.

Vial contains sterile, non-pyrogenic cobalt stabilizer solution
of 200 mcg cobalt chloride 6-hydrate stabilizer solution
in 2 mL of Water for Injection. Use as directed in package
insert. Store at 15°-25°C (59°-77°F). Do not freeze.

Manufactured for: GE Healthcare
Medi-Physics, Inc.
Arlington Heights, IL 60004, 1-800-292-8514
By: GE Healthcare AS, Oslo, Norway

1193054 USA

Exp.:

Lot:

PRINCIPAL DISPLAY PANEL - Kit Carton Label

GE Healthcare

CERETEC™
Technetium Tc99m Exametazime Injection

NDC 17156-025-05

Five-unit package

Storage: Store the kit at 15°-25°C (59°-77°F).
After reconstitution with Technetium Tc99m,
store at 20°-25°C (68°-77°F). Do not freeze.

Use appropriate radiation shielding.
Not for use in humans until technetium
Tc99m is added.

For intravenous use as directed.
For Dosage and Administration:
See Package Insert.

Contents: Each package contains the following:

Five Ceretec vials. Each vial contains a lyophilized form of 0.5 mg exametazime.
7.6 mcg, stannous chloride dihydrate (minimum stannous tin
0.6 mcg, maximum total stannous and stannic tin 4 mcg per vial) and
4.5 mg sodium chloride.

Five Cobalt (II) chloride 6-hydrate vials. Each vial contains
sterile, non-pyrogenic cobalt stabilizer solution of 200 mcg
cobalt chloride 6-hydrate stabilizer solution in 2 mL of Water for Injection.

Ten radiation labels

One package insert

For preparation of Technetium Tc99m Exametazime
Injection see package insert.